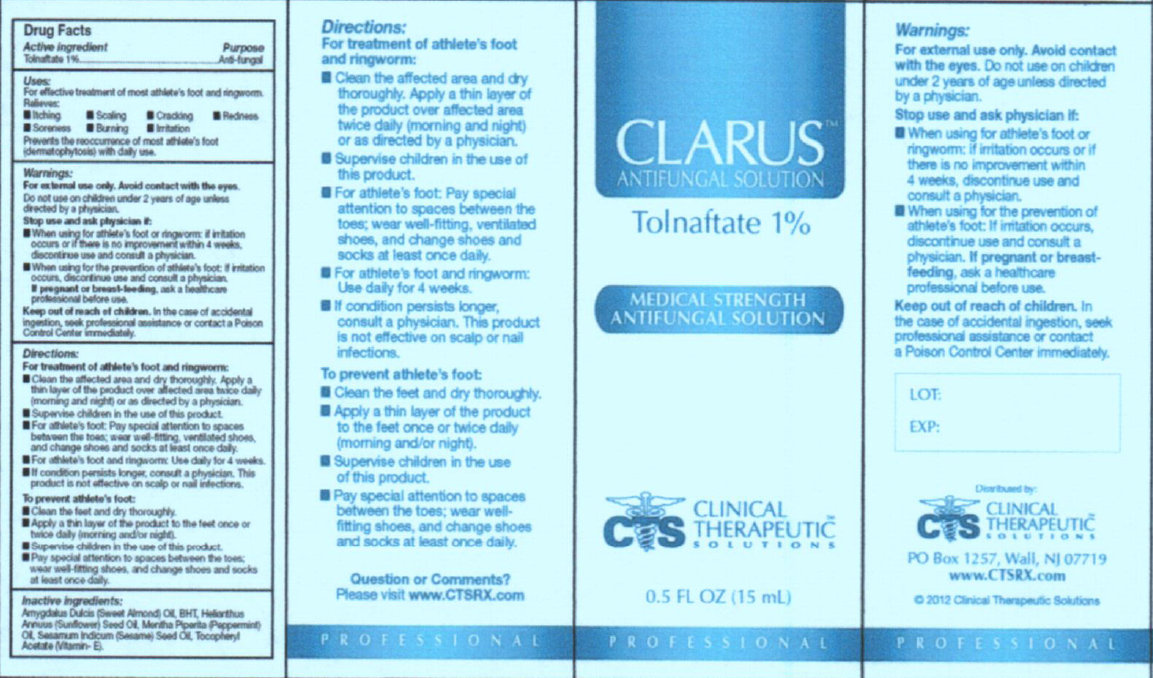 DRUG LABEL: CLARUS Antifungal
NDC: 44577-002 | Form: SOLUTION
Manufacturer: Clinical Therapeutic Solutions
Category: otc | Type: HUMAN OTC DRUG LABEL
Date: 20231105

ACTIVE INGREDIENTS: TOLNAFTATE 1 g/100 mL
INACTIVE INGREDIENTS: ALMOND OIL; BUTYLATED HYDROXYTOLUENE; SUNFLOWER OIL; PEPPERMINT OIL; SESAME OIL; .ALPHA.-TOCOPHEROL ACETATE

CLARUS Antifungal

Active Ingredient

Tolnaftate 1 %

Purpose

Anti-fungal

Uses:

For effective treatment of most athlete's foot and ringworm. Relieves:

Prevents the reoccurrence of most athlete's foot with daily use.

- Itching
- Scaling
- Cracking
- Redness
- Soreness
- Burning
- Irritation

Warnings

For external use only. Avoid contact with eyes.

Do not use

on children under 2 years of age unless directed by a physician.

Stop use and ask physician if:

- When using for athlete's foot or ringworm: if irritation occurs or if there is no improvement within 4 weeks, discontinue use and consult a physician.
- When using for prevention of athlete's foot: If irritation occurs, discontinue use and consult a physician.

If pregnant or breast-feeding,

ask a healthcare professional before use.

Keep out of reach of children

In the case of accidental ingestion, seek professional assistance or contact a Poison Control Center immediately.

Directions:

For treatment of athlete's foot and ringworm:

If condition persists longer, consult a physician. This product is not effective on scalp or nail infections.

To prevent athlete's foot:

- Clean the affected area and dry thoroughly. Apply a thin layer of the product over affected area twice daily (morning and night) or as directed by a physician.
- Supervise children in the use of this product.
- For athlete's foot: Pay special attention to spaces between the toes; wear well-fitting, ventilated shoes, and change shoes and socks at least once daily.
- For athlete's foot and ringworm: Use daily for 4 weeks.

- Clean the feet and dry thoroughly.
- Apply a thin layer of the product to the feet once or twice daily (morning and/or night).
- Supervise children in the use of this product.
- Pay special attention to spaces between the toes; wear well-fitting shoes, and change shoes and socks at least once daily.

Questions or Comments?

Please visit www.CTSRX.com

Inactive ingredients:

Amygdalus Dulcis (Sweet Almond) Oil, BHT, Helianthus Annuus (Sunflower) Seed Oil, Mentha Piperita (Peppermint) Oil, Sesamum Indicum (Sesame) Seed Oil, Tocopheryl Acetate (Vitamin E).

PACKAGE LABEL

CLARUS ANTIFUNGAL SOLUTION Tolnaftate 1% MEDICAL STRENGTH ANTIFUNGAL SOLUTION CLINICAL THERAPEUTIC SOLUTIONS PO Box 1257, Wall, NJ 07719 0.5 FL OZ (15 mL)